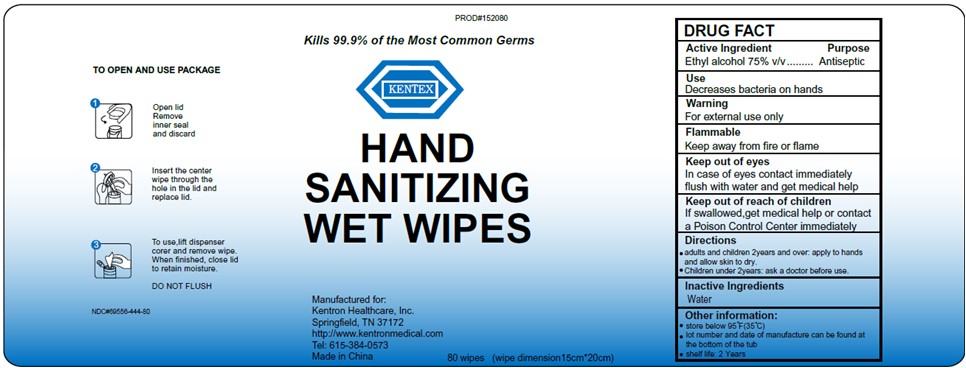 DRUG LABEL: KENTEX Hand Sanitizing Wet Wipes
NDC: 69556-444 | Form: SOLUTION
Manufacturer: Kentron Healthcare, Inc.
Category: otc | Type: HUMAN OTC DRUG LABEL
Date: 20211102

ACTIVE INGREDIENTS: ALCOHOL 3.4 mL/1 1
INACTIVE INGREDIENTS: WATER

69556-444-80 Kentex wipes

ACTIVE INGREDIENT

Ethyl Alcohol 75% v/v

Purpose

Antiseptic

Use

Decrease bacteria on hands

Warnings

For external use only

Flammable. Keep away from fire or flame

keep out of eyes. In case of eye contact, immediately flush with water and get medical help

Keep out of reach of children. If swallowed, get medical help or contact a poison control immediately

Directions

- Adults and children 2 years and over: apply to hands and allow skin to dry
- Children under 2 years: ask a doctor before use

Inactive ingredients

Water